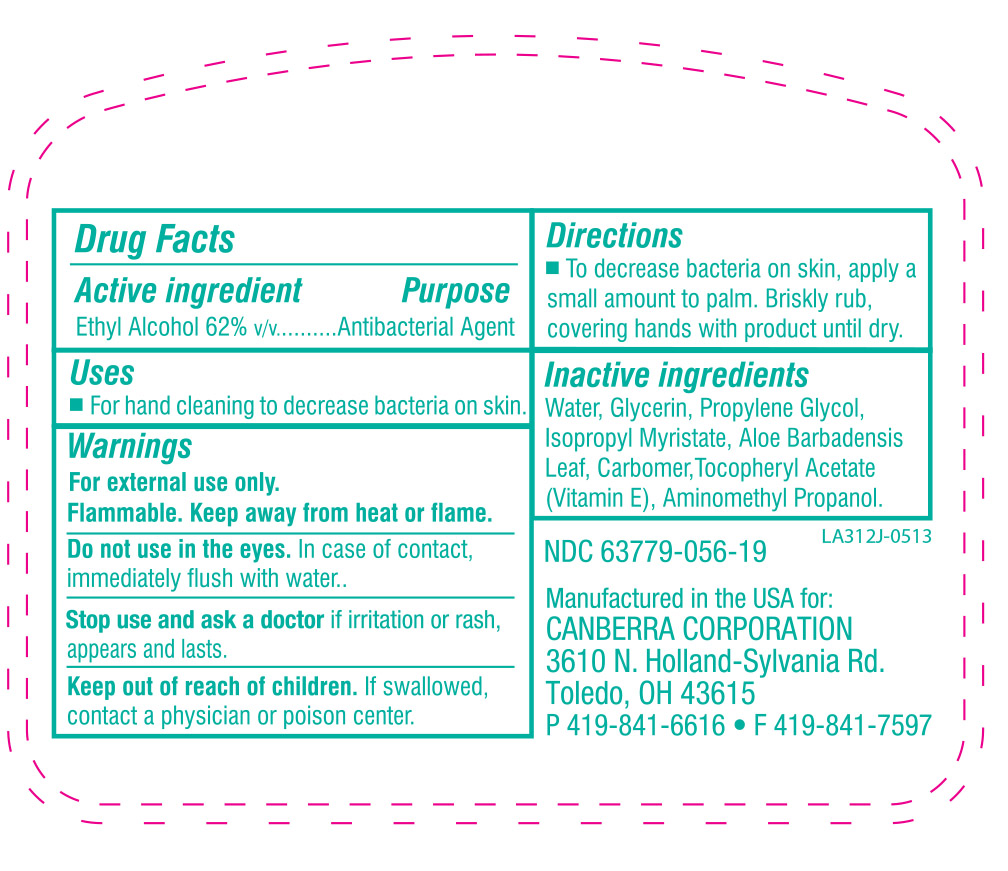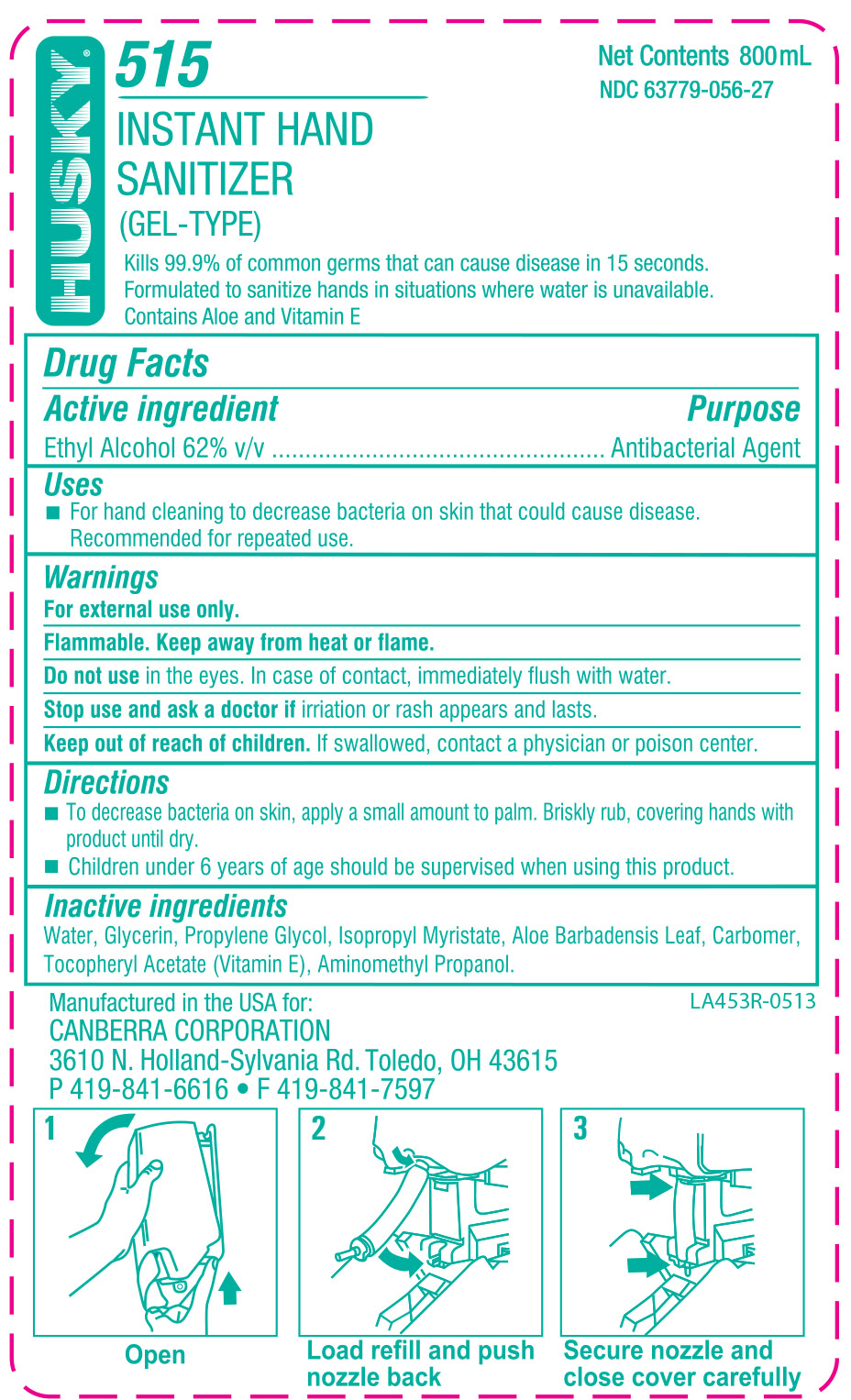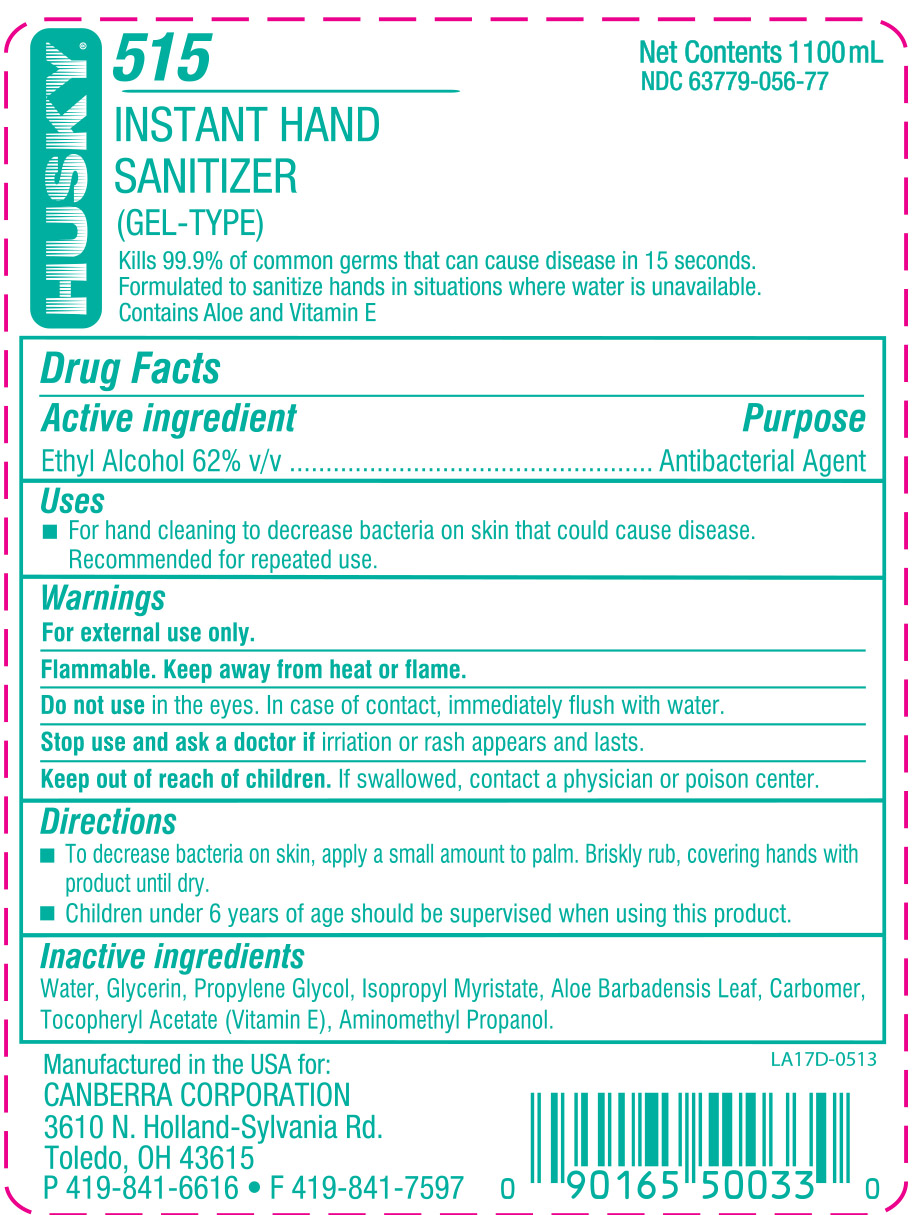 DRUG LABEL: Husky Instant Hand Sanitizer
NDC: 63779-056 | Form: SOLUTION
Manufacturer: Canberra Corporation
Category: otc | Type: HUMAN OTC DRUG LABEL
Date: 20140221

ACTIVE INGREDIENTS: ALCOHOL 62 mL/100 mL
INACTIVE INGREDIENTS: POLYACRYLIC ACID (250000 MW); WATER; GLYCERIN; PROPYLENE GLYCOL; ISOPROPYL MYRISTATE; AMINOMETHYLPROPANOL; ALOE VERA LEAF; .ALPHA.-TOCOPHEROL ACETATE, DL-

Husky Instant Hand Sanitizer

WARNINGS

For external use only.

Flammable. Keep away from heat or flame.

Do not use in the eyes. In case of contact, immediately flush with water.

Stop use and ask a doctor if irritation or rash appears and lasts.

Keep out of reach of children. If swallowed, contact a physician or poison center.

ACTIVE INGREDIENT

Ethyl Alcohol 62% v/v.........Antibacterial Agent

Keep out of reach of children. If swallowed, contact a physician or poison center.

INACTIVE INGREDIENT

Water, Glycerin, Propylene Glycol, Isopropyl Mryistate, Aloe Barbadensis Leaf, Carbomer, Tocopheryl Acetate (Vitamin E), Aminomethyl Propanol

DOSAGE AND ADMINISTRATION

63779-056-77 & 63779-056-27:

To decrease bacteria on skin, apply a small amount to palm. Briskly rub, covering hands with product until dry.

Children under 6 years of age should be supervised when using this product.

63779-056-87 & 63779-056-19:

To decrease bacteria on skin, apply a small amount to palm. Briskly rub, covering hands with product until dry.

PURPOSE

63779-056-77 & 63779-056-27: For hand cleaning to decrease bacteria on skin that could cause disease. Recommended for repeated use.

63779-056-87: For handwashing to decrease bacteria on skin.

63779-056-19: For hand cleaning to decrease bacteria on skin.

INDICATIONS AND USAGE

For hand cleaning to decrease bacteria on skin that could cause disease. Recommended for repeated use.

Do not use in the eyes. In case of contact, immediately flush with water.

Stop use and ask a doctor if irritation or rash appears and lasts.

Keep out of reach of children. If swallowed, contact a physician or poison center.

PACKAGE LABEL

63779-056-19.jpg

PACKAGE LABEL

63779-056-27.jpg

PACKAGE LABEL

63779-056-77.jpg

PACKAGE LABEL

63779-056-87.jpg